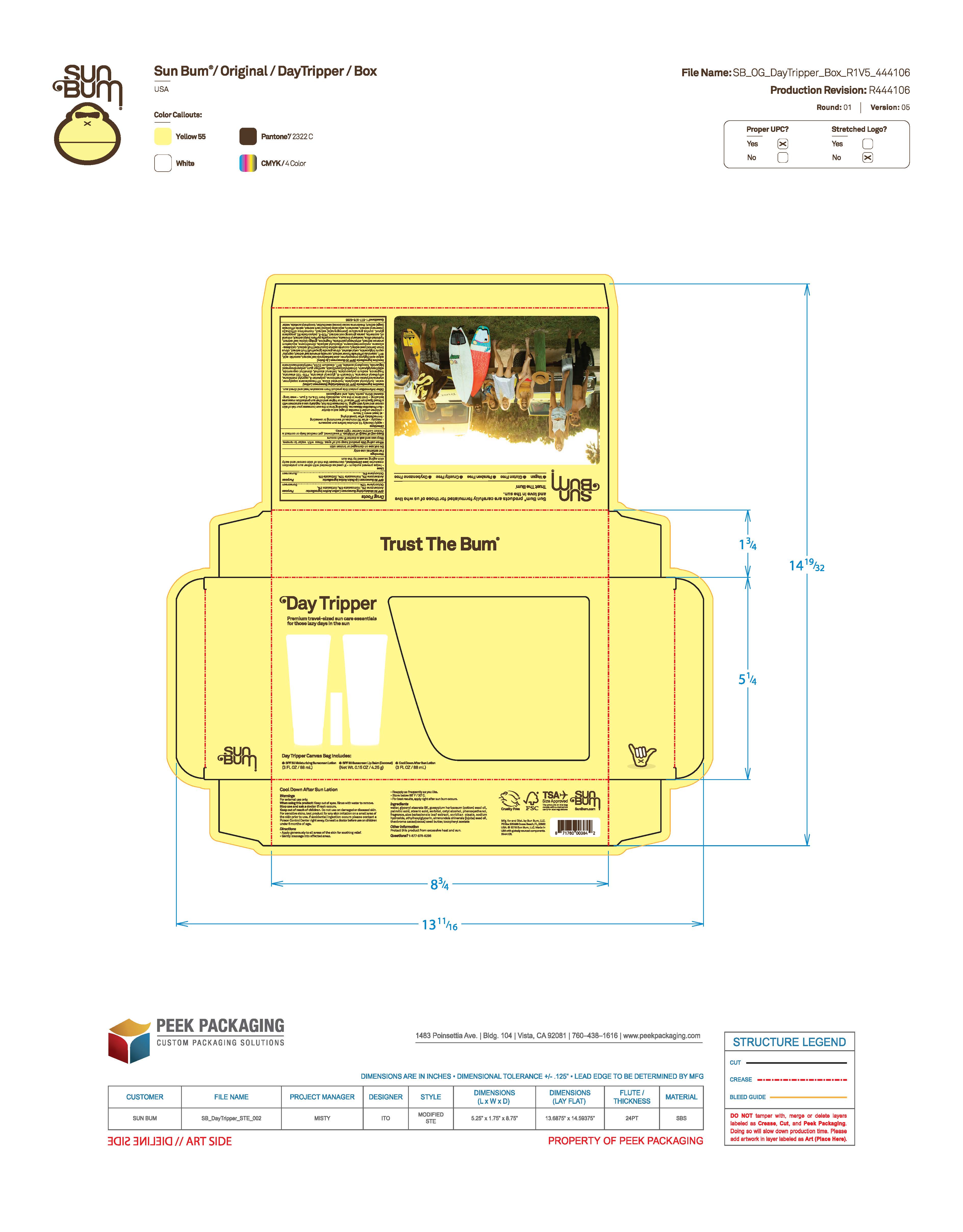 DRUG LABEL: Sun Bum Day Tripper - SPF 30 Sunscreen Lip Balm (Coconut) 0.15 OZ
NDC: 69039-815 | Form: STICK
Manufacturer: Sun Bum, LLC
Category: otc | Type: HUMAN OTC DRUG LABEL
Date: 20250820

ACTIVE INGREDIENTS: AVOBENZONE 30 mg/1 g; HOMOSALATE 100 mg/1 g; OCTISALATE 50 mg/1 g; OCTOCRYLENE 80 mg/1 g
INACTIVE INGREDIENTS: BHT; CETYL ALCOHOL; ASCORBIC ACID; ETHYLHEXYL PALMITATE; ISOSTEARYL LINOLEATE; MACROCYSTIS PYRIFERA (KELP); MINERAL OIL; CERESIN; PEG-8; POLYSORBATE 80; POMEGRANATE; ROSEMARY; SACCHARIN; WILLOW BARK; SAGE; THEOBROMA CACAO (COCOA) SEED BUTTER; .ALPHA.-TOCOPHEROL ACETATE; WATER; LEMON PEEL; GRAPEFRUIT; DIISOBUTYL ADIPATE; EQUISETUM ARVENSE WHOLE; ALOE BARBADENSIS LEAF; GINKGO BILOBA LEAF; PROPYLENE GLYCOL; DIMETHICONE; PANAX GINSENG ROOT; CAMELLIA SINENSIS LEAF; ADIPIC ACID/DIGLYCOL CROSSPOLYMER (20000 MPA.S); CALENDULA OFFICINALIS FLOWER; CYCLOHEXASILOXANE; CUCUMIS SATIVUS (CUCUMBER) FRUIT; CYCLOPENTASILOXANE; HYDRATED SILICA; CAPRYLIC/CAPRIC TRIGLYCERIDE

Sun Bum Day Tripper and Sun Bum Day Tripper Amazon - SPF 30 Sunscreen Lip Balm (Coconut) 0.15 OZ

Active Ingredients

AVOBENZONE 3%, HOMOSALATE 10%, OCTISALATE 5%, OCTOCRYLENE 8%

Purpose

Sunscreen

Uses

• helps prevent sunburn • if used as directed with other sun protection measures, (see Directions) decreases the risk of skin cancer and early skin aging caused by the sun

Warnings

For external use only

Do not use on damaged or broken skin

When using this product keep out of eyes. Rinse with water to remove.

Stop use and ask a doctor if rash occurs

Keep out of reach of children. If swallowed, get medical help or contact a Poison Control Center right away.

Warnings

Keep Out Of Reach Of Children

Directions

• apply liberally 15 minutes before sun exposure

• reapply: • after 80 minutes of swimming or sweating • immediately after towel drying • at least every 2 hours

• children under 6 months of age: ask a doctor

• Sun Protection Measures. Spending time in the sun increases your risk of skin cancer and early skin aging. To decrease this risk, regularly use a sunscreen with a Broad Spectrum SPF value of 15 or higher and other sun protection measures including:

• limit time in the sun, especially from 10 a.m.- 2 p.m.

• wear long-sleeved shirts, pants, hats and sunglasses

Directions

• apply liberally 15 minutes before sun exposure

Other Information

protect this product from excessive heat and direct sun

Inactive Ingredients

ADIPIC ACID/DIGLYCOL CROSSPOLYMER, ALOE BARBADENSIS LEAF EXTRACT, ASCORBIC ACID, BHT, CALENDULA OFFICINALIS FLOWER EXTRACT, CAMELLIA SINENSIS LEAF EXTRACT, CAPRYLIC/CAPRIC TRIGLYCERIDE, CETYL ALCOHOL, CITRUS GRANDIS (GRAPEFRUIT) FRUIT EXTRACT, CITRUS LIMON (LEMON) PEEL EXTRACT, CUCUMIS SATIVUS (CUCUMBER) FRUIT EXTRACT, CYCLOHEXASILOXANE, CYCLOPENTASILOXANE, DIISOBUTYL ADIPATE, DIMETHICONE, EQUISETUM ARVENSE EXTRACT, ETHYLHEXYL PALMITATE, FRAGRANCE, GINKGO BILOBA LEAF EXTRACT, HYDRATED SILICA, ISOSTEARYL LINOLEATE, MACROCYSTIS PYRIFERA (KELP) EXTRACT, MINERAL OIL, OZOKERITE, PANAX GINSANG ROOT EXTRACT, PEG-8, POLYSORBATE 80, PROPYLENE GLYCOL, PUNICA GRANATUM POMEGRANATE) EXTRACT, ROSMARINUS OFFICINALIS (ROSEMARY) EXTRACT, SACCHARIN, SALIX ALBA (WILLOW) BARK EXTRACT, SALVIA OFFICINALIS (SAGE) EXTRACT, THEOBROMA CACAO (COCOA) SEED BUTTER, TOCOPHEROL ACETATE, WATER

Questions?

1-877-978-6286